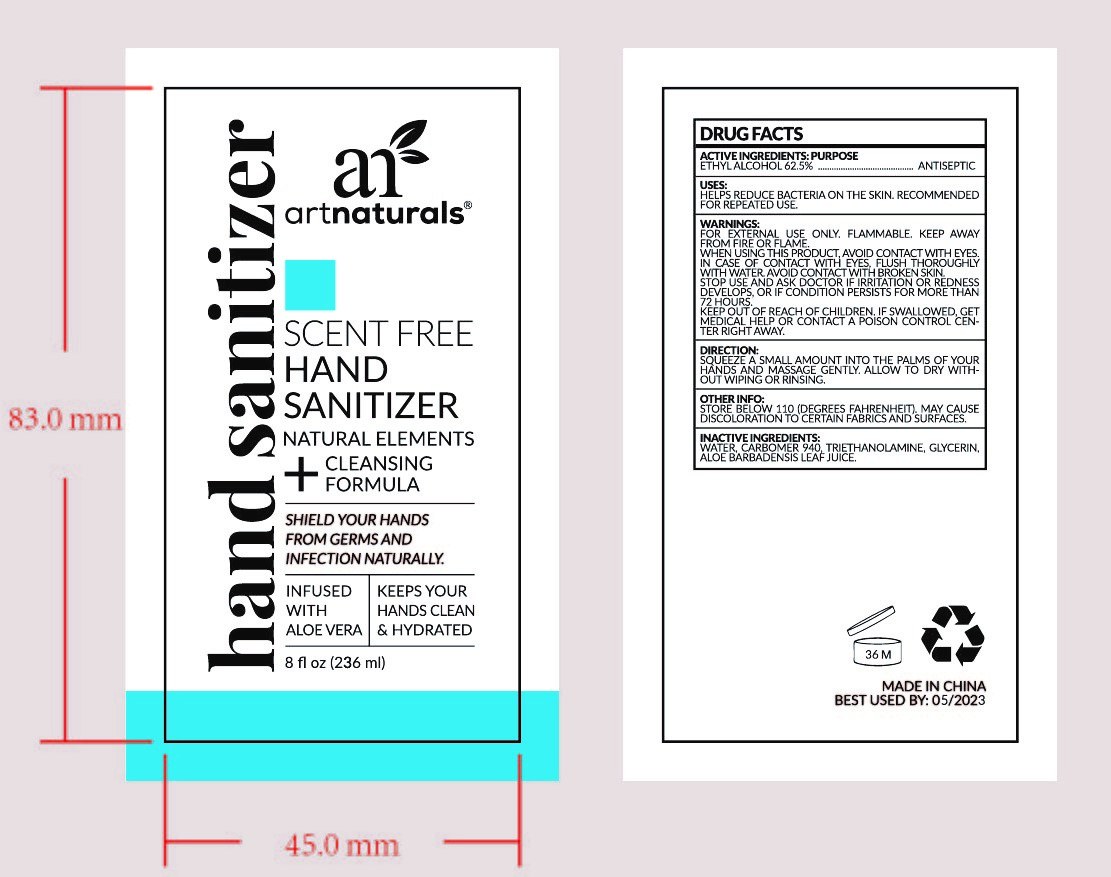 DRUG LABEL: HAND SANITIZER
NDC: 47993-213 | Form: GEL
Manufacturer: NINGBO JIANGBEI OCEAN STAR TRADING CO.,LTD
Category: otc | Type: HUMAN OTC DRUG LABEL
Date: 20201029

ACTIVE INGREDIENTS: ALCOHOL 62.5 g/112 mL
INACTIVE INGREDIENTS: TRIETHANOLAMINE BENZOATE 3 g/112 mL; WATER 19.5 g/112 mL; CARBOMER 940 12 g/112 mL; GLYCERIN 2 g/112 mL; ALOE VERA LEAF 1 g/112 mL

47993-213

Active ingredients

Ethyl Alcohol 62.5%

PURPOSE

Antiseptic

Uses:
Helps reduce bacteria on the skin. Recommended for repeated use.

Uses:

Helps reduce bacteria on the skin. Recommended for repeated use.

Warnings:

For external use only.Flammable. Keep away from fire or flame.

When using this product. Avoid contact with eyes. In case of contact with eyes, flush thoroughly with water. Avoid contact with broken skin.

Stop use and ask doctor if irritation or redness develops, or if condition persists for more than 72 hours.

Keep out of reach of children. If swallowed, get medical help or contact a poison control center right away.

Directions:

Squeeze small amount into the palms or your hands and massage gently. Allow to dry without wiping or rinsing.

Directions:

Squeeze small amount into the palms or your hands and massage gently. Allow to dry without wiping or rinsing.

Other Information

Store below 110F(Degrees Fahrenheit). May cause discoloration to certain fabrics and surfaces.

Inactive ingredients

Water，Carbomer 940，Triethanolamine，Glycerin，Aloe Barbadensis leaf juice